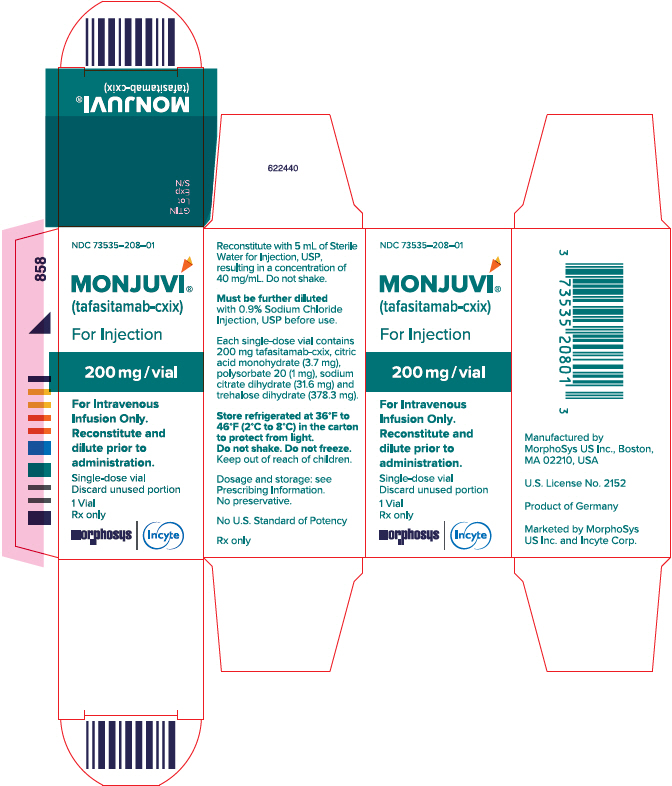 DRUG LABEL: MONJUVI
NDC: 73535-208 | Form: INJECTION, POWDER, LYOPHILIZED, FOR SOLUTION
Manufacturer: Incyte Corporation
Category: prescription | Type: HUMAN PRESCRIPTION DRUG LABEL
Date: 20260202

ACTIVE INGREDIENTS: TAFASITAMAB 200 mg/5 mL
INACTIVE INGREDIENTS: TRISODIUM CITRATE DIHYDRATE 31.6 mg/5 mL; CITRIC ACID MONOHYDRATE 3.7 mg/5 mL; TREHALOSE DIHYDRATE 378.3 mg/5 mL; POLYSORBATE 20 1 mg/5 mL

HIGHLIGHTS OF PRESCRIBING INFORMATION

These highlights do not include all the information needed to use MONJUVI safely and effectively. See full prescribing information for MONJUVI.
MONJUVI®(tafasitamab-cxix) for injection, for intravenous use
Initial U.S. Approval: 2020

1 INDICATIONS AND USAGE

MONJUVI is a CD19-directed cytolytic antibody indicated in combination with lenalidomide for the treatment of adult patients with relapsed or refractory diffuse large B-cell lymphoma (DLBCL) not otherwise specified, including DLBCL arising from low grade lymphoma, and who are not eligible for autologous stem cell transplant (ASCT).

This indication is approved under accelerated approval based on overall response rate. Continued approval for this indication may be contingent upon verification and description of clinical benefit in a confirmatory trial(s). (1)

2 DOSAGE AND ADMINISTRATION

- Administer premedications prior to starting MONJUVI. (2.2)
- The recommended dosage of MONJUVI is 12 mg/kg as an intravenous infusion according to the following dosing schedule: (2.1)
  - Cycle 1: Days 1, 4, 8, 15 and 22 of the 28-day cycle.
  - Cycles 2 and 3: Days 1, 8, 15 and 22 of each 28-day cycle.
  - Cycle 4 and beyond: Days 1 and 15 of each 28-day cycle.
- Administer MONJUVI in combination with lenalidomide for a maximum of 12 cycles and then continue MONJUVI as monotherapy until disease progression or unacceptable toxicity. (2.1)
- See Full Prescribing Information for instructions on preparation and administration. (2.3, 2.4)

3 DOSAGE FORMS AND STRENGTHS

For injection: 200 mg of tafasitamab-cxix as lyophilized powder in single-dose vial for reconstitution.(3)

4 CONTRAINDICATIONS

None.

5 WARNINGS AND PRECAUTIONS

- Infusion-Related Reactions: Monitor patients frequently during infusion. Interrupt or discontinue infusion based on severity. (2.3, 5.1)
- Myelosuppression: Monitor complete blood counts. Manage using dose modifications and growth factor support. Interrupt or discontinue MONJUVI based on severity. (2.3, 5.2)
- Infections: Bacterial, fungal and viral infections can occur during and following MONJUVI. Monitor patients for infections. (2.3, 5.3)
- Embryo-Fetal Toxicity: May cause fetal harm. Advise females of reproductive potential of the potential risk to a fetus and use of effective contraception. (5.4)

6 ADVERSE REACTIONS

The most common adverse reactions (≥20%) are neutropenia, fatigue, anemia, diarrhea, thrombocytopenia, cough, pyrexia, peripheral edema, respiratory tract infection, and decreased appetite. (6.1)

To report SUSPECTED ADVERSE REACTIONS, contact MORPHOSYS US INC. at 1-844-667-1992 or FDA at 1-800-FDA-1088 or www.fda.gov/medwatch .

8 USE IN SPECIFIC POPULATIONS

Lactation: Advise not to breastfeed. (8.2)

FULL PRESCRIBING INFORMATION

1 INDICATIONS AND USAGE

MONJUVI, in combination with lenalidomide, is indicated for the treatment of adult patients with relapsed or refractory diffuse large B-cell lymphoma (DLBCL) not otherwise specified, including DLBCL arising from low grade lymphoma, and who are not eligible for autologous stem cell transplant (ASCT).

This indication is approved under accelerated approval based on overall response rate [see Clinical Studies (14)] . Continued approval for this indication may be contingent upon verification and description of clinical benefit in a confirmatory trial(s).

2 DOSAGE AND ADMINISTRATION

2.1 Recommended Dosage

The recommended dose of MONJUVI is 12 mg/kg based on actual body weight administered as an intravenous infusion according to the dosing schedule in Table 1.

Administer MONJUVI in combination with lenalidomide 25 mg for a maximum of 12 cycles, then continue MONJUVI as monotherapy until disease progression or unacceptable toxicity [see Clinical Studies (14)]. Refer to the lenalidomide prescribing information for lenalidomide dosage recommendations.

Table 1: MONJUVI Dosing Schedule
Cycle [Each treatment cycle is 28-days.] | Dosing Schedule
Cycle 1 | Days 1, 4, 8, 15 and 22
Cycles 2 and 3 | Days 1, 8, 15 and 22
Cycle 4 and beyond | Days 1 and 15

MONJUVI should be administered by a healthcare professional with immediate access to emergency equipment and appropriate medical support to manage infusion-related reactions (IRRs) [see Warnings and Precautions (5.1)] .

2.2 Recommended Premedications

Administer premedications 30 minutes to 2 hours prior to starting MONJUVI infusion to minimize infusion-related reactions [see Warnings and Precautions (5.1)]. Premedications may include acetaminophen, histamine H1receptor antagonists, histamine H2receptor antagonists, and/or glucocorticosteroids.

For patients not experiencing infusion-related reactions during the first 3 infusions, premedication is optional for subsequent infusions.

If a patient experiences an infusion-related reaction, administer premedications before each subsequent infusion.

2.3 Dosage Modifications for Adverse Reactions

The recommended dosage modifications for adverse reactions are summarized in Table 2.

Table 2: Dosage Modifications for Adverse Reactions
Adverse Reaction | Severity | Dosage Modification
Infusion-related reactions [see Warnings and Precautions (5.1)] | Grade 2 (moderate) | - Interrupt infusion immediately and manage signs and symptoms. - Once signs and symptoms resolve or reduce to Grade 1, resume infusion at no more than 50% of the rate at which the reaction occurred. If the patient does not experience further reaction within 1 hour and vital signs are stable, the infusion rate may be increased every 30 minutes as tolerated to the rate at which the reaction occurred.
Infusion-related reactions [see Warnings and Precautions (5.1)] | Grade 3 (severe) | - Interrupt infusion immediately and manage signs and symptoms. - Once signs and symptoms resolve or reduce to Grade 1, resume infusion at no more than 25% of the rate at which the reaction occurred. If the patient does not experience further reaction within 1 hour and vital signs are stable, the infusion rate may be increased every 30 minutes as tolerated to a maximum of 50% of the rate at which the reaction occurred. - If after rechallenge the reaction returns, stop the infusion immediately.
Infusion-related reactions [see Warnings and Precautions (5.1)] | Grade 4 (life-threatening) | - Stop the infusion immediately and permanently discontinue MONJUVI.
Myelosuppression [see Warnings and Precautions (5.2)] | Platelet count of 50,000/ mcL or less | - Withhold MONJUVI and lenalidomide and monitor complete blood count (CBC) weekly until platelet count is 50,000/mcL or higher. - Resume MONJUVI at the same dose and lenalidomide at a reduced dose. Refer to lenalidomide prescribing information for dosage modifications.
Myelosuppression [see Warnings and Precautions (5.2)] | Neutrophil count of 1,000/ mcL or less for at least 7 days OR Neutrophil count of 1,000/ mcL or less with an increase of body temperature to 100.4°F (38°C) or higher OR Neutrophil count less than 500/mcL | - Withhold MONJUVI and lenalidomide and monitor CBC weekly until neutrophil count is 1,000/ mcL or higher. - Resume MONJUVI at the same dose and lenalidomide at a reduced dose. Refer to lenalidomide prescribing information for dosage modifications.

2.4 Preparation and Administration

Reconstitute and dilute MONJUVI prior to infusion.

Reconstitution

1. Calculate the dose (mg) and determine the number of vials needed.
2. Reconstitute each 200 mg MONJUVI vial with 5 mL Sterile Water for Injection, USP with the stream directed toward the wall of each vial to obtain a final concentration of 40 mg/mL tafasitamab-cxix.
3. Gently swirl the vial(s) until completely dissolved. Do not shake or swirl vigorously. Complete dissolution may take up to 5 minutes.
4. Visually inspect the reconstituted solution for particulate matter or discoloration. The reconstituted solution should appear as a colorless to slightly yellow solution. Discard the vial(s) if the solution is cloudy, discolored, or contains visible particles.
5. Use the reconstituted MONJUVI solution immediately. If needed, store the reconstituted solution in the vial for a maximum of 12 hours either refrigerated at 36°F to 46°F (2°C to 8°C) or room temperature at 68°F to 77°F (20°C to 25°C) before dilution. Protect from light during storage.

Dilution

1. Determine the volume (mL) of the 40 mg/mL reconstituted MONJUVI solution needed based on the required dose.
2. Remove a volume equal to the required MONJUVI solution from a 250 mL 0.9% Sodium Chloride Injection, USP infusion bag and discard it.
3. Withdraw the necessary amount of MONJUVI and slowly dilute in the infusion bag that contains the 0.9% Sodium Chloride Injection, USP to a final concentration of 2 mg/mL to 8 mg/mL. Discard any unused portion of MONJUVI remaining in the vial.
4. Gently mix the intravenous bag by slowly inverting the bag. Do not shake. Visually inspect the infusion bag with the diluted MONJUVI infusion solution for particulate matter and discoloration prior to administration.
5. If not used immediately, store the diluted MONJUVI infusion solution refrigerated for up to 18 hours at 36°F to 46°F (2°C to 8°C) and/or at room temperature for up to 12 hours at 68°F to 77°F (20°C to 25°C). The room temperature storage includes time for infusion. Protect from light during storage.

Do not shake or freeze the reconstituted or diluted infusion solutions.

Administration

- Administer MONJUVI as an intravenous infusion.
  - For the first infusion, use an infusion rate of 70 mL/h for the first 30 minutes, then, increase the rate so that the infusion is administered within 1.5 to 2.5 hours.
  - Administer all subsequent infusions within 1.5 to 2 hours.
- Infuse the entire contents of the bag containing MONJUVI.
- Do not co-administer other drugs through the same infusion line.
- No incompatibilities have been observed between MONJUVI with infusion containers made of polypropylene (PP), polyvinylchloride (PVC), polyethylene (PE), polyethylenterephthalate (PET), or glass and infusion sets made of polyurethane (PUR) or PVC.

3 DOSAGE FORMS AND STRENGTHS

For injection: 200 mg of tafasitamab-cxix as white to slightly yellowish lyophilized powder in single-dose vial for reconstitution and further dilution.

4 CONTRAINDICATIONS

None.

5 WARNINGS AND PRECAUTIONS

5.1 Infusion-Related Reactions

MONJUVI can cause infusion-related reactions [see Adverse Reactions (6.1)] . In L-MIND, infusion-related reactions occurred in 6% of the 81 patients. Eighty percent of infusion-related reactions occurred during cycle 1 or 2. Signs and symptoms included fever, chills, rash, flushing, dyspnea, and hypertension. These reactions were managed with temporary interruption of the infusion and/or with supportive medication.

Premedicate patients prior to starting MONJUVI infusion [see Dosage and Administration (2.2)] . Monitor patients frequently during infusion. Based on the severity of the infusion-related reaction, interrupt or discontinue MONJUVI [see Dosage and Administration (2.3)] . Institute appropriate medical management.

5.2 Myelosuppression

MONJUVI can cause serious or severe myelosuppression, including neutropenia, thrombocytopenia, and anemia [see Adverse Reactions (6.1)] . In L-MIND, Grade 3 neutropenia occurred in 25% of patients, thrombocytopenia in 12%, and anemia in 7%. Grade 4 neutropenia occurred in 25% and thrombocytopenia in 6%. Neutropenia led to treatment discontinuation in 3.7% of patients.

Monitor CBC prior to administration of each treatment cycle and throughout treatment. Monitor patients with neutropenia for signs of infection. Consider granulocyte colony-stimulating factor administration. Withhold MONJUVI based on the severity of the adverse reaction [see Dosage and Administration (2.3)]. Refer to the lenalidomide prescribing information for dosage modifications.

5.3 Infections

Fatal and serious infections, including opportunistic infections, occurred in patients during treatment with MONJUVI and following the last dose [see Adverse Reactions (6.1)].

In L-MIND, 73% of the 81 patients developed an infection. The most frequent infections were respiratory tract infection (24%), urinary tract infection (17%), bronchitis (16%), nasopharyngitis (10%) and pneumonia (10%). Grade 3 or higher infection occurred in 30% of the 81 patients. The most frequent grade 3 or higher infection was pneumonia (7%). Infection-related deaths were reported in 2.5% of the 81 patients.

Monitor patients for signs and symptoms of infection and manage infections as appropriate.

5.4 Embryo-Fetal Toxicity

Based on its mechanism of action, MONJUVI may cause fetal B-cell depletion when administered to a pregnant woman. Advise pregnant women of the potential risk to a fetus. Advise females of reproductive potential to use effective contraception during treatment with MONJUVI and for at least 3 months after the last dose [see Use in Specific Populations (8.1, 8.3)] .

MONJUVI is initially administered in combination with lenalidomide. The combination of MONJUVI with lenalidomide is contraindicated in pregnant women because lenalidomide can cause birth defects and death of the unborn child. Refer to the lenalidomide prescribing information on use during pregnancy.

6 ADVERSE REACTIONS

The following clinically significant adverse reactions are described elsewhere in the labeling:

- Infusion-related reactions [see Warnings and Precautions (5.1)]
- Myelosuppression [see Warnings and Precautions (5.2)]
- Infections [see Warnings and Precautions (5.3)]

6.1 Clinical Trials Experience

Because clinical trials are conducted under widely varying conditions, adverse reaction rates observed in clinical trials of a drug cannot be directly compared to rates in other clinical trials of another drug and may not reflect the rates observed in practice.

Relapsed or Refractory Diffuse Large B-Cell Lymphoma

The safety of MONJUVI was evaluated in L-MIND [see Clinical Studies (14)]. Patients (n=81) received MONJUVI 12 mg/kg intravenously in combination with lenalidomide for a maximum of 12 cycles, followed by MONJUVI as monotherapy until disease progression or unacceptable toxicity as follows:

- Cycle 1: Days 1, 4, 8, 15 and 22 of the 28-day cycle;
- Cycles 2 and 3: Days 1, 8, 15 and 22 of each 28-day cycle;
- Cycles 4 and beyond: Days 1 and 15 of each 28-day cycle.

Among patients who received MONJUVI, 57% were exposed for 6 months or longer, 42% were exposed for greater than one year, and 24% were exposed for greater than two years.

Serious adverse reactions occurred in 52% of patients who received MONJUVI. Serious adverse reactions in ≥6% of patients included infections (26%), including pneumonia (7%), and febrile neutropenia (6%). Fatal adverse reactions occurred in 5% of patients who received MONJUVI, including cerebrovascular accident (1.2%), respiratory failure (1.2%), progressive multifocal leukoencephalopathy (1.2%) and sudden death (1.2%).

Permanent discontinuation of MONJUVI or lenalidomide due to an adverse reaction occurred in 25% of patients and permanent discontinuation of MONJUVI due to an adverse reaction occurred in 15%. The most frequent adverse reactions which resulted in permanent discontinuation of MONJUVI were infections (5%), nervous system disorders (2.5%), respiratory, thoracic and mediastinal disorders (2.5%).

Dosage interruptions of MONJUVI or lenalidomide due to an adverse reaction occurred in 69% of patients and dosage interruption of MONJUVI due to an adverse reaction occurred in 65%. The most frequent adverse reactions which required a dosage interruption of MONJUVI were blood and lymphatic system disorders (41%), and infections (27%).

The most common adverse reactions (≥ 20%) were neutropenia, fatigue, anemia, diarrhea, thrombocytopenia, cough, pyrexia, peripheral edema, respiratory tract infection, and decreased appetite.

Table 3 summarizes the adverse reactions in L-MIND.

Table 3: Adverse Reactions (≥10%) in Patients with Relapsed or Refractory Diffuse Large B-Cell Lymphoma Who Received MONJUVI in L-MIND
Adverse Reaction | MONJUVI (N=81)
Adverse Reaction | All Grades (%) | Grade 3 or 4 (%)
Blood and lymphatic system disorders
Neutropenia | 51 | 49
Anemia | 36 | 7
Thrombocytopenia | 31 | 17
Febrile neutropenia | 12 | 12
General disorders and administration site conditions
Fatigue [Fatigue includes asthenia and fatigue] | 38 | 3.7
Pyrexia | 24 | 1.2
Peripheral edema | 24 | 0
Gastrointestinal disorders
Diarrhea | 36 | 1.2
Constipation | 17 | 0
Abdominal pain [Abdominal pain includes abdominal pain, abdominal pain lower, and abdominal pain upper] | 15 | 1.2
Nausea | 15 | 0
Vomiting | 15 | 0
Respiratory, thoracic and mediastinal disorders
Cough | 26 | 1.2
Dyspnea | 12 | 1.2
Infections
Respiratory tract infection [Respiratory tract infection includes: lower respiratory tract infection, upper respiratory tract infection, respiratory tract infection] | 24 | 4.9
Urinary tract infection [Urinary tract infection includes: urinary tract infection, Escherichia urinary tract infection, urinary tract infection bacterial, urinary tract infection enterococcal] | 17 | 4.9
Bronchitis | 16 | 1.2
Metabolism and nutrition disorders
Decreased appetite | 22 | 0
Hypokalemia | 19 | 6
Musculoskeletal and connective tissue disorders
Back pain | 19 | 2.5
Muscle spasms | 15 | 0
Skin and subcutaneous tissue disorders
Rash [Rash includes rash, rash maculo-papular, rash pruritic, rash erythematous , rash pustular] | 15 | 2.5
Pruritus | 10 | 1.2

Clinically relevant adverse reactions in <10% of patients who received MONJUVI were:

- Blood and lymphatic system disorders: lymphopenia (6%)
- General disorders and administration site conditions: infusion-related reaction (6%)
- Infections: sepsis (4.9%)
- Investigations: weight decreased (4.9%)
- Musculoskeletal and connective tissue disorders: arthralgia (9%), pain in extremity (9%), musculoskeletal pain (2.5%)
- Neoplasms benign, malignant and unspecified: basal cell carcinoma (1.2%)
- Nervous system disorders:headache (9%), paresthesia (7%), dysgeusia (6%)
- Respiratory, thoracic and mediastinal disorders:nasal congestion (4.9%), exacerbation of chronic obstructive pulmonary disease (1.2%)
- Skin and subcutaneous tissue disorders:erythema (4.9%), alopecia (2.5%), hyperhidrosis (2.5%)

Table 4 summarizes the laboratory abnormalities in L-MIND.

Table 4: Select Laboratory Abnormalities (>20%) Worsening from Baseline in Patients with Relapsed or Refractory Diffuse Large B-Cell Lymphoma Who Received MONJUVI in L-MIND
Laboratory Abnormality | MONJUVI [The denominator used to calculate the rate was 74 based on the number of patients with a baseline value and at least one post-treatment value.]
Laboratory Abnormality | All Grades (%) | Grade 3 or 4 (%)
Chemistry
Glucose increased | 49 | 5
Calcium decreased | 47 | 1.4
Gamma glutamyl transferase increased | 34 | 5
Albumin decreased | 26 | 0
Magnesium decreased | 22 | 0
Urate increased | 20 | 7
Phosphate decreased | 20 | 5
Creatinine increased | 20 | 1.4
Aspartate aminotransferase increased | 20 | 0
Coagulation
Activated partial thromboplastin time increased | 46 | 4.1

6.2 Immunogenicity

As with all therapeutic proteins, there is the potential for immunogenicity. The detection of antibody formation is highly dependent on the sensitivity and specificity of the assays. Additionally, the observed incidence of antibody (including neutralizing antibody) positivity in an assay may be influenced by several factors, including assay methodology, sample handling, timing of sample collection, concomitant medications, and underlying disease. For these reasons, comparison of the incidence of antibodies in the studies described below with the incidence of antibodies in other studies or to other tafasitamab products may be misleading.

Overall, no treatment-emergent or treatment-boosted anti-tafasitamab antibodies were observed. No clinically meaningful differences in the pharmacokinetics, efficacy, or safety profile of tafasitamab-cxix were observed in 2.5% of 81 patients with relapsed or refractory DLBCL with pre-existing anti-tafasitamab antibodies in L-MIND.

8 USE IN SPECIFIC POPULATIONS

8.1 Pregnancy

Risk Summary

Based on its mechanism of action, MONJUVI may cause fetal B-cell depletion when administered to a pregnant woman [see Clinical Pharmacology (12.1)] . There are no available data on MONJUVI use in pregnant women to evaluate for a drug-associated risk. Animal reproductive toxicity studies have not been conducted with tafasitamab-cxix.

In the U.S. general population, the estimated background risk of major birth defects and miscarriage in clinically recognized pregnancies is 2% to 4% and 15% to 20%, respectively.

MONJUVI is administered in combination with lenalidomide for up to 12 cycles. Lenalidomide can cause embryo-fetal harm and is contraindicated for use in pregnancy. Refer to the lenalidomide prescribing information for additional information. Lenalidomide is only available through a REMS program.

Clinical Considerations

Fetal/Neonatal Adverse Reactions

Immunoglobulin G (IgG) monoclonal antibodies are transferred across the placenta. Based on its mechanism of action, MONJUVI may cause depletion of fetal CD19 positive immune cells. Defer administering live vaccines to neonates and infants exposed to tafasitamab-cxix in utero until a hematology evaluation is completed.

Data

Animal Data

Animal reproductive studies have not been conducted with tafasitamab-cxix. Tafasitamab-cxix is an IgG antibody and thus has the potential to cross the placental barrier permitting direct fetal exposure and depleting fetal B lymphocytes.

8.2 Lactation

Risk Summary

There are no data on the presence of tafasitamab-cxix in human milk or the effects on the breastfed child or milk production. Maternal immunoglobulin G is known to be present in human milk. The effects of local gastrointestinal exposure and limited systemic exposure in the breastfed infant to MONJUVI are unknown. Because of the potential for serious adverse reactions in the breastfed child, advise women not to breastfeed during treatment with MONJUVI and for at least 3 months after the last dose. Refer to lenalidomide prescribing information for additional information.

8.3 Females and Males of Reproductive Potential

MONJUVI can cause fetal B-cell depletion when administered to a pregnant woman [see Use in Specific Populations (8.1)].

Pregnancy Testing

Refer to the prescribing information for lenalidomide for pregnancy testing requirements prior to initiating the combination of MONJUVI with lenalidomide.

Contraception

Females

Advise females of reproductive potential to use effective contraception during treatment with MONJUVI and for at least 3 months after the last dose. Additionally, refer to the lenalidomide prescribing information for additional recommendations for contraception.

Males

Refer to the lenalidomide prescribing information for recommendations.

8.4 Pediatric Use

The safety and effectiveness of MONJUVI in pediatric patients have not been established.

8.5 Geriatric Use

Among 81 patients who received MONJUVI and lenalidomide in L-MIND, 72% were 65 years and older, while 38% were 75 years and older. Clinical studies of MONJUVI did not include sufficient numbers of patients aged 65 and older to determine whether effectiveness differs compared to that of younger subjects. Patients 65 years and older had more serious adverse reactions (57%) than younger patients (39%).

11 DESCRIPTION

Tafasitamab-cxix is a humanized CD19-directed cytolytic monoclonal antibody that contains an IgG1/2 hybrid Fc-domain with 2 amino acid substitutions to modify the Fc-mediated functions of the antibody. It is produced by recombinant DNA technology in mammalian cells (Chinese hamster ovary). Tafasitamab-cxix has a molecular weight of approximately 150 kDa.

MONJUVI (tafasitamab-cxix) for injection is supplied as a sterile, preservative-free, white to slightly yellowish lyophilized powder in a single-dose vial for intravenous use after reconstitution and further dilution. After reconstitution with 5 mL of Sterile Water for Injection, USP, the resulting concentration is 40 mg/mL with a pH of 6.0. Each single-dose vial contains 200 mg tafasitamab-cxix, citric acid monohydrate (3.7 mg), polysorbate 20 (1 mg), sodium citrate dihydrate (31.6 mg) and trehalose dihydrate (378.3 mg).

12 CLINICAL PHARMACOLOGY

12.1 Mechanism of Action

Tafasitamab-cxix is an Fc-modified monoclonal antibody that binds to CD19 antigen expressed on the surface of pre-B and mature B lymphocytes and on several B-cell malignancies, including diffuse large B-cell lymphoma (DLBCL).

Upon binding to CD19, tafasitamab-cxix mediates B-cell lysis through apoptosis and immune effector mechanisms, including antibody-dependent cellular cytotoxicity (ADCC) and antibody-dependent cellular phagocytosis (ADCP).

In studies conducted in vitro in DLBCL tumor cells, tafasitamab-cxix in combination with lenalidomide resulted in increased ADCC activity compared to tafasitamab-cxix or lenalidomide alone.

12.2 Pharmacodynamics

Tafasitamab-cxix reduced peripheral blood B cell counts by 97% after eight days of treatment in patients with relapsed or refractory DLBCL. Nadir, with a reduction of 100%, was reached within 16 weeks of treatment.

12.3 Pharmacokinetics

Mean trough concentrations (± standard deviation) were 179 (± 53) μg/mL following administration of MONJUVI at 12 mg/kg on Days 1, 8, 15, and 22 in Cycle 1-3 (plus an additional dose on Cycle 1 Day 4), and 153 (± 68) μg/mL following administration of MONJUVI at 12 mg/kg on Days 1 and 15 from Cycle 4 onwards. Overall maximum tafasitamab-cxix serum concentrations were 483 (±109) μg/mL.

Distribution

The total volume of distribution for tafasitamab-cxix was 9.3 L (95% CI: 8.6, 10 L).

Elimination

The clearance of tafasitamab-cxix was 0.41 L/day (CV: 32%) and terminal elimination half-life was 17 days (95% CI: 15, 18 days).

Specific Populations

Bodyweight (40 to 163 kg) has a significant effect on the pharmacokinetics of tafasitamab-cxix, with higher clearance and volume of distribution expected with higher body weight. No clinically meaningful differences in the pharmacokinetics of tafasitamab-cxix were observed based on age (16 to 90 years), sex, mild to moderate renal impairment (CLcr 30-89 mL/min estimated by the Cockcroft-Gault equation), and mild hepatic impairment (total bilirubin ≤ ULN and AST > ULN, or total bilirubin 1 to 1.5 times ULN and any AST). The effect of severe renal impairment to end-stage renal disease (CLcr < 30 mL/min), moderate to severe hepatic impairment (total bilirubin > 1.5 times ULN and any AST), and race/ethnicity on tafasitamab-cxix pharmacokinetics is unknown.

Drug Interaction Studies

No clinically meaningful differences in tafasitamab-cxix pharmacokinetics were observed when used concomitantly with lenalidomide.

13 NONCLINICAL TOXICOLOGY

13.1 Carcinogenesis, Mutagenesis, Impairment of Fertility

Carcinogenicity and genotoxicity studies have not been conducted with tafasitamab-cxix.

Fertility studies have not been conducted with tafasitamab-cxix.

In the 13-week repeat-dose general toxicity study in cynomolgus monkeys, no adverse effects on male and female reproductive organs were observed up to the highest dose tested, 100 mg/kg/week (approximately 9 times the human exposure based on AUC at the clinical dose of 12 mg/kg/week).

14 CLINICAL STUDIES

The efficacy of MONJUVI in combination with lenalidomide followed by MONJUVI as monotherapy was evaluated in L-MIND, an open-label, multicenter, single arm trial (NCT02399085). Eligible patients had relapsed or refractory DLBCL after 1 to 3 prior systemic therapies, including a CD20-directed cytolytic antibody, and were not candidates for high dose chemotherapy (HDC) followed by autologous stem cell transplantation (ASCT). Patients received MONJUVI 12 mg/kg intravenously in combination with lenalidomide (25 mg orally on Days 1 to 21 of each 28-day cycle) for a maximum of 12 cycles, followed by MONJUVI as monotherapy until disease progression or unacceptable toxicity as follows:

- Cycle 1: Days 1, 4, 8, 15 and 22 of the 28-day cycle;
- Cycles 2 and 3: Days 1, 8, 15 and 22 of each 28-day cycle;
- Cycles 4 and beyond: Days 1 and 15 of each 28-day cycle.

Of the 71 patients with DLBCL confirmed by central laboratory who received the combination therapy, the median age was 71 years (range: 41 to 86 years); 55% were males, and 100% had received a prior CD20-containing therapy. Race was collected in 92% of patients; of these, 95% were White, and 3% were Asian. The median number of prior therapies was two; 49% had one prior line of treatment, and 51% had 2 to 4 prior lines. Thirty-two patients (45%) were refractory to their last prior therapy and 30 (42%) were refractory to rituximab. Nine patients (13%) had received prior ASCT. The primary reasons patients were not candidates for ASCT included age (47%), refractoriness to salvage chemotherapy (27%), comorbidities (13%) and refusal of high dose chemotherapy/ASCT (13%).

Efficacy was established based on best overall response rate, defined as the proportion of complete and partial responders, and duration of response, as assessed by an Independent Review Committee using the International Working Group Response Criteria (Cheson, 2007). Results are summarized in Table 5.

Table 5: Efficacy Results in L-MIND
 | N = 71
Best overall response rate, n (%) | 39 (55%)
(95% CI) | (43%, 67%)
Complete response rate | 37%
Partial response rate | 18%
Duration of Response
Median (range) in months [Kaplan Meier estimates] | 21.7 (0, 24)

16 HOW SUPPLIED/STORAGE AND HANDLING

MONJUVI (tafasitamab-cxix) for injection is a sterile, preservative-free, white to slightly yellowish lyophilized powder for reconstitution supplied as a 200 mg single-dose vial.

Each 200 mg vial is individually packaged in a carton (NDC 73535–208–01).

STORAGE AND HANDLING

Store refrigerated at 36°F to 46°F (2°C to 8°C) in the original carton to protect from light. Do not shake. Do not freeze.

17 PATIENT COUNSELING INFORMATION

Advise the patient to read the FDA-approved patient labeling (Patient Information).

Infusion-Related Reactions

Advise patients to contact their healthcare provider if they experience signs and symptoms of infusion-related reactions [see Warnings and Precautions (5.1)] .

Myelosuppression

Inform patients about the risk of myelosuppression. Advise patients to immediately contact their healthcare provider for a fever of 100.4°F (38°C) or greater or signs or symptoms of bruising or bleeding. Advise patients of the need for periodic monitoring of blood counts [see Warnings and Precautions (5.2)] .

Infections

Inform patients about the risk of infections. Advise patients to immediately contact their healthcare provider for a fever of 100.4°F (38°C) or greater or signs or symptoms of infection [see Warnings and Precautions (5.3)] .

Embryo-Fetal Toxicity

- Advise pregnant women of the potential risk to a fetus. Advise females of reproductive potential to inform their healthcare provider of a known or suspected pregnancy [see Warnings and Precautions (5.4), Use in Specific Population (8.1)].
- Advise females of reproductive potential to use effective contraception during treatment with MONJUVI and for at least 3 months after the last dose [see Use in Specific Populations (8.3)] .
- Advise patients that lenalidomide has the potential to cause fetal harm and has specific requirements regarding contraception, pregnancy testing, blood and sperm donation, and transmission in sperm. Lenalidomide is only available through a REMS program [see Use in Specific Populations (8.1, 8.3)].

Lactation

Advise women not to breastfeed during treatment with MONJUVI and for at least 3 months after the last dose [see Use in Specific Populations (8.2)].

Manufactured by:
MORPHOSYS US INC.
Boston, MA 02210
U.S. License No. 2152

Marketed by:
MORPHOSYS US INC. and INCYTE Corporation.
MONJUVI is a registered trademark of MorphoSys AG

Copyright © 2020 MorphoSys AG. All rights reserved.
Product of Germany

PATIENT INFORMATION
MONJUVI®(mon-JOO-vee)
(tafasitamab-cxix)
for injection

What is MONJUVI?
MONJUVI is a prescription medicine given with lenalidomide to treat adults with certain types of diffuse large B-cell lymphoma (DLBCL) that has come back (relapsed) or that did not respond to previous treatment (refractory) and who cannot receive a stem cell transplant.
It is not known if MONJUVI is safe and effective in children.

Before you receive MONJUVI, tell your healthcare provider about all of your medical conditions, including if you:

- have an active infection or have had one recently.
- are pregnant or plan to become pregnant. MONJUVI may harm your unborn baby. You should not become pregnant during treatment with MONJUVI. Do not receive treatment with MONJUVI in combination with lenalidomide if you are pregnant because lenalidomide can cause birth defects and death of your unborn baby.
  - You should use an effective method of birth control (contraception) during treatment and for at least 3 months after your last dose of MONJUVI.
  - Tell your healthcare provider right away if you become pregnant or think you may be pregnant during treatment with MONJUVI.
- are breastfeeding or plan to breastfeed. It is not known if MONJUVI passes into your breastmilk. Do not breastfeed during treatment and for at least 3 months after your last dose of MONJUVI.

You should also read the lenalidomide Medication Guide for important information about pregnancy, contraception, and blood and sperm donation.
Tell your healthcare provider about all the medicines you take,including prescription and over-the-counter medicines, vitamins, and herbal supplements.

How will I receive MONJUVI?

- MONJUVI will be given to you by your healthcare provider as an intravenous (IV) infusion into one of your veins.
- Your healthcare provider will give you medicines before each infusion to decrease your chance of infusion reactions. If you do not have any reactions, your healthcare provider may decide that you do not need these medicines with later infusions.
- Each treatment cycle of MONJUVI lasts for 28 days.
- Your healthcare provider may need to delay or completely stop treatment with MONJUVI if you have severe side effects.
- Your healthcare provider will decide how many treatments you need.
- If you miss any appointments, call your healthcare provider as soon as possible to reschedule your appointment.

What are the possible side effects of MONJUVI?
MONJUVI may cause serious side effects, including:

- Infusion reactions.Your healthcare provider will monitor you for infusion reactions during your infusion of MONJUVI. Tell your healthcare provider right away if you get fever, chills, flushing, headache, or shortness of breath during an infusion of MONJUVI.
- Low blood cell counts(platelets, red blood cells, and white blood cells). Low blood cell counts are common with MONJUVI, but can also be serious or severe. Your healthcare provider will monitor your blood counts during treatment with MONJUVI. Tell your healthcare provider right away if you get a fever of 100.4°F (38°C) or above, or any bruising or bleeding.
- Infections.Serious infections, including infections that can cause death, have happened in people during treatment with MONJUVI and after the last dose. Tell your healthcare provider right away if you get a fever of 100.4°F (38°C) or above, or develop any signs or symptoms of an infection.

The most common side effects of MONJUVI include:

- feeling tired or weak
- diarrhea
- cough
- fever

- swelling of lower legs or hands
- respiratory tract infection
- decreased appetite

These are not all the possible side effects of MONJUVI.
Call your doctor for medical advice about side effects. You may report side effects to FDA at 1-800-FDA-1088.

General information about the safe and effective use of MONJUVI.
Medicines are sometimes prescribed for purposes other than those listed in this Patient Information. If you would like more information about MONJUVI, talk with your healthcare provider. You can ask your healthcare provider for information about MONJUVI that is written for health professionals.

What are the ingredients in MONJUVI?
Active ingredient:tafasitamab-cxix.
Inactive ingredients:citric acid monohydrate, polysorbate 20, sodium citrate dihydrate, and trehalose dihydrate.
Manufactured by: MORPHOSYS US INC., Boston, MA 02210, U.S. License No. 2152,
Marketed by: MORPHOSYS US INC. and INCYTE Corporation.
MONJUVI is a registered trademark of MorphoSys AG. © 2020 MorphoSys AG. All rights reserved.
For more information call MorphoSys US Inc., at 1-844-667-1992 or go to www.MONJUVI.com.

This Patient Information has been approved by the U.S. Food and Drug Administration.

Issued: JUN 2021

PRINCIPAL DISPLAY PANEL - 200 mg Vial Carton

NDC 73535–208–01

MONJUVI®
(tafasitamab-cxix)

For Injection

200 mg/vial

For Intravenous
Infusion Only.
Reconstitute and
dilute prior to
administration.

Single-dose vial
Discard unused portion

1 Vial
Rx only

morphosys | Incyte